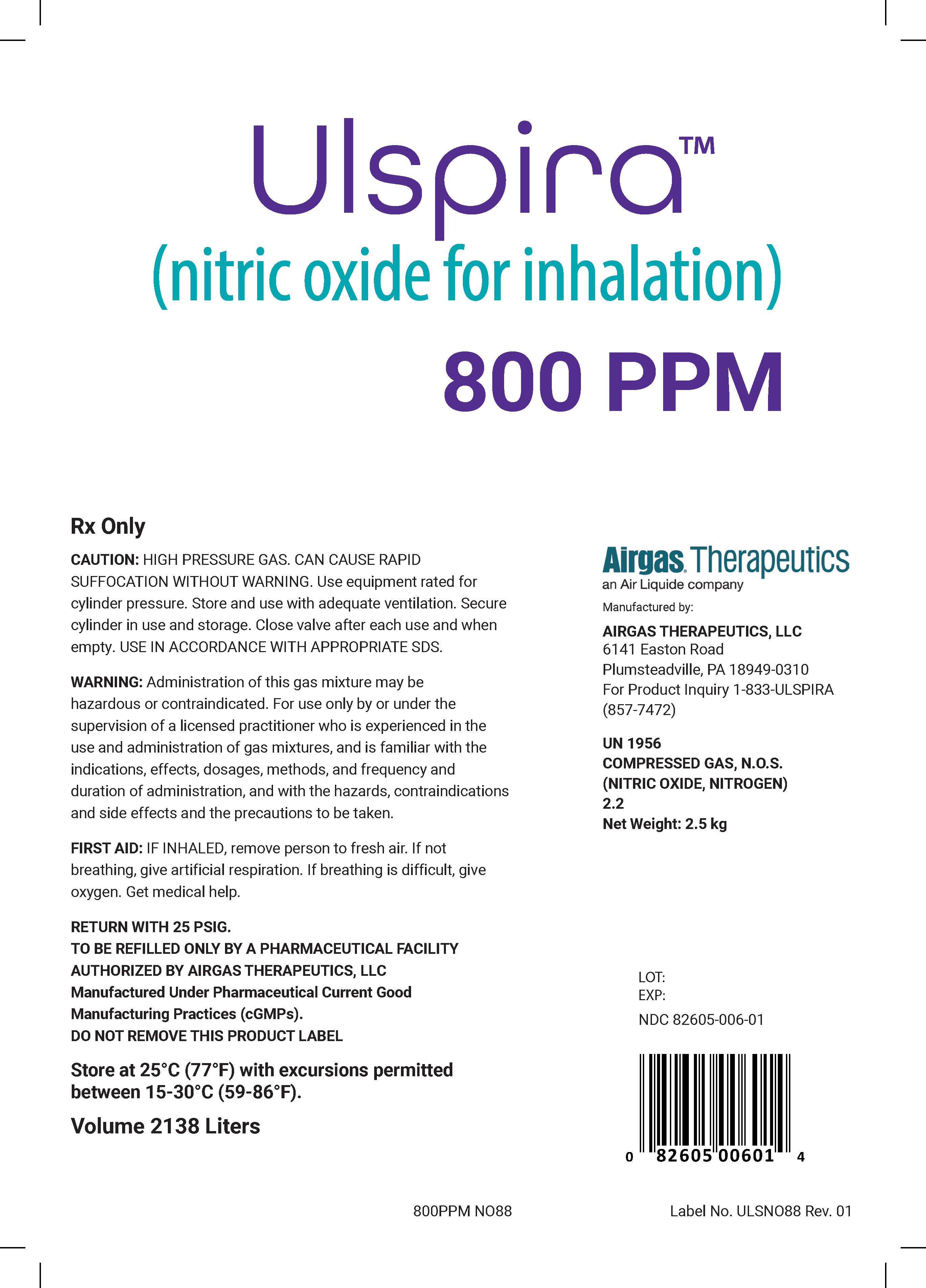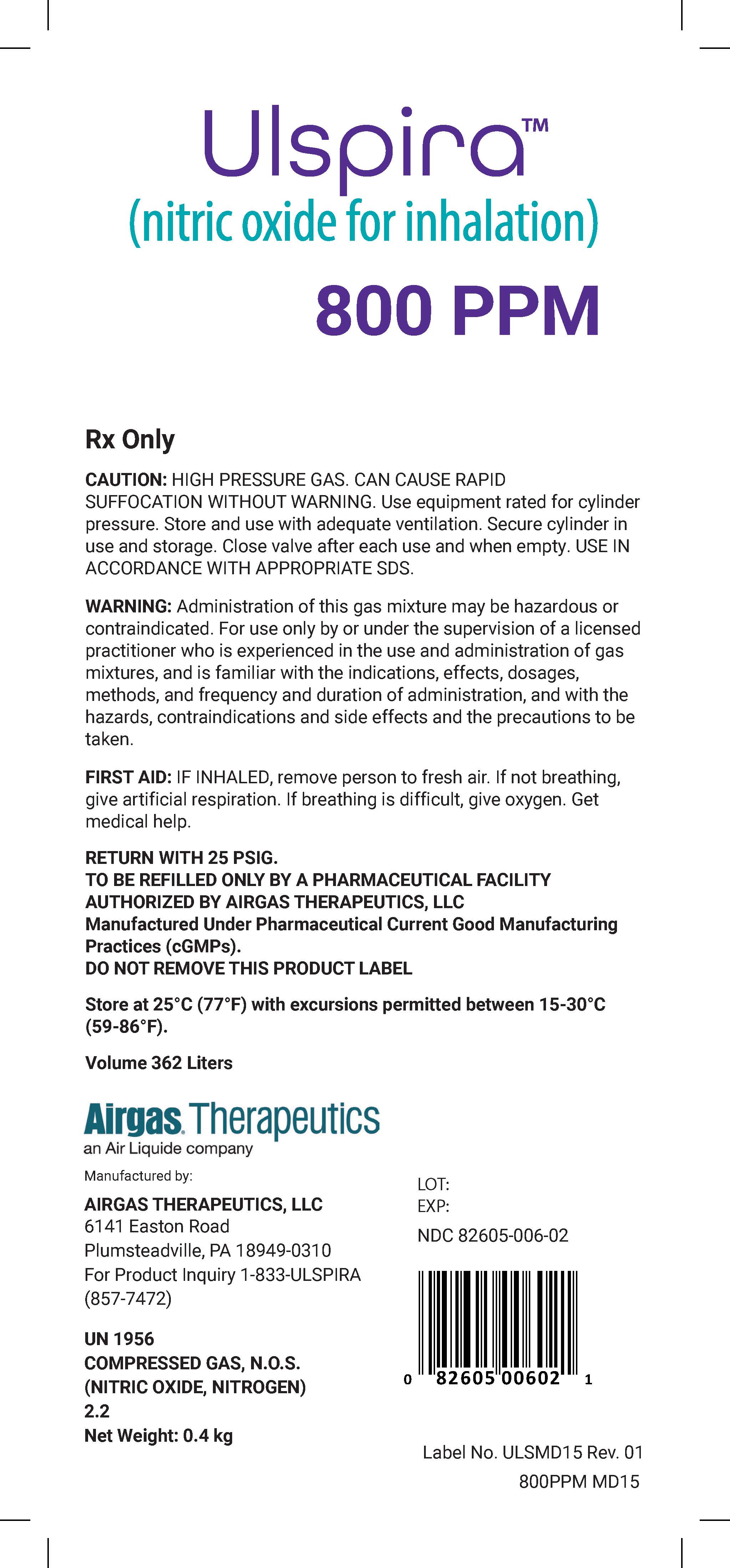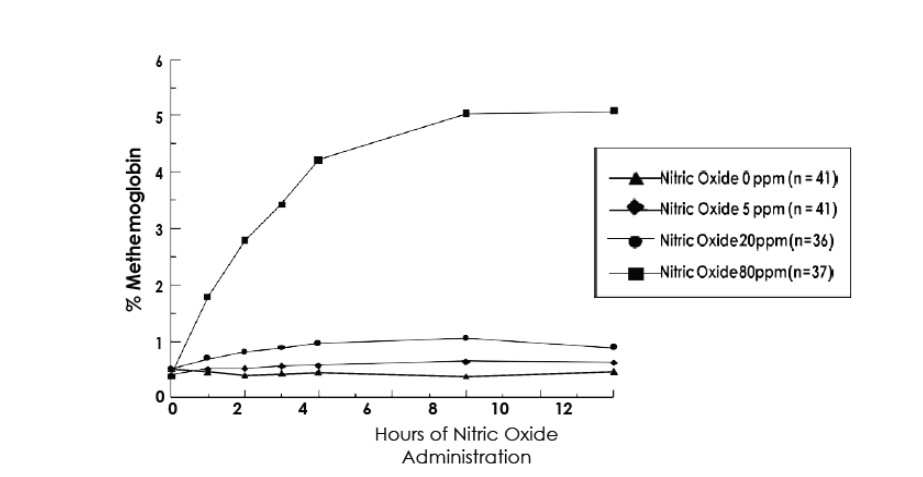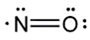 DRUG LABEL: Ulspira
NDC: 82605-006 | Form: GAS
Manufacturer: Airgas Therapeutics, LLC
Category: prescription | Type: HUMAN PRESCRIPTION DRUG LABEL
Date: 20250716

ACTIVE INGREDIENTS: NITRIC OXIDE 0.8 mL/100 L
INACTIVE INGREDIENTS: NITROGEN 999.2 mL/100 L

HIGHLIGHTS OF PRESCRIBING INFORMATION
These highlights do not include all the information needed to use ULSPIRA™ safely and effectively. See full prescribing information for ULSPIRA.
ULSPIRA™ (nitric oxide) gas, for inhalation Initial U.S. Approval: 1999

1 INDICATIONS AND USAGE

ULSPIRA is a vasodilator indicated to improve oxygenation and reduce the need for extracorporeal membrane oxygenation in term and near- term (>34 weeks gestation) neonates with hypoxic respiratory failure associated with clinical or echocardiographic evidence of pulmonary hypertension in conjunction with ventilatory support and other appropriate agents.

2 DOSAGE AND ADMINISTRATION

The recommended dose is 20 ppm, maintained for up to 14 days or until the underlying oxygen desaturation has resolved (2.1).

Doses greater than 20 ppm are not recommended (2.1, 5.2)

Administration:

- Avoid abrupt discontinuation (2.2, 5.1).

3 DOSAGE FORMS AND STRENGTHS

ULSPIRA (nitric oxide) is a gas available in a 800 ppm concentration (3).

4 CONTRAINDICATIONS

Neonates dependent on right-to-left shunting of blood (4).

5 WARNINGS AND PRECAUTIONS

Rebound: Abrupt discontinuation of ULSPIRA may lead to worsening oxygenation and increasing pulmonary artery pressure (5.1).

Methemoglobinemia: Methemoglobin increases with the dose of nitric oxide; following discontinuation or reduction of nitric oxide, methemoglobin levels return to baseline over a period of hours (5.2).

Elevated NO2Levels: Monitor NO2levels (5.3).

Heart Failure: In patients with pre-existing left ventricular dysfunction, ULSPIRA may increase pulmonary capillary wedge pressure leading to pulmonary edema (5.4).

6 ADVERSE REACTIONS

The most common adverse reaction is hypotension. (6).

To report SUSPECTED ADVERSE REACTIONS, contact Airgas Therapeutics at 1-833-ULSPIRA (857-7472) and http://www.ulspira.com/ or FDA at 1-800-FDA-1088 or www.fda.gov/medwatch.

7 DRUG INTERACTIONS

Nitric oxide donor compounds may increase the risk of developing methemoglobinemia (7).

FULL PRESCRIBING INFORMATION

1 INDICATIONS AND USAGE

ULSPIRA™ is indicated to improve oxygenation and reduce the need for extracorporeal membrane oxygenation in term and near-term (>34 weeks gestation) neonates with hypoxic respiratory failure associated with clinical or echocardiographic evidence of pulmonary hypertension in conjunction with ventilatory support and other appropriate agents.

2 DOSAGE AND ADMINISTRATION

2.1 Dosage

Term and near-term neonates with hypoxic respiratory failure

The recommended dose of ULSPIRA is 20 ppm. Maintain treatment up to 14 days or until the underlying oxygen desaturation has resolved and the neonate is ready to be weaned from ULSPIRA therapy.

Doses greater than 20 ppm are not recommended [see Warnings and Precautions (5.2)].

2.2 Administration

Nitric Oxide Delivery Systems

ULSPIRA must be administered using a calibrated FDA-cleared Nitric Oxide Delivery System (NODS). There are various FDA-cleared NODS; refer to the NODS labeling to determine which NODS to use with this drug product and for needed information on training and technical support for users of this drug product with the NODS. Do not use ULSPIRA with Inomax DSIR Plus and DSIR Plus MRI NODS.

Do not use ULSPIRA in the MRI suite.

Keep available a backup battery power supply and an independent reserve nitric oxide delivery system to address power and system failures .

Monitoring

Measure methemoglobin within 4-8 hours after initiation of treatment with ULSPIRA and periodically throughout treatment [see Warnings and Precautions (5.2)].

Monitor for PaO2 and inspired NO2 during ULSPIRA administration [see Warnings and Precautions 5.3)].

Weaning and Discontinuation

Avoid abrupt discontinuation of ULSPIRA [see Warnings and Precautions (5.1)].To wean ULSPIRA, downtitrate in several steps, pausing several hours at each step to monitor for hypoxemia.

3 DOSAGE FORMS AND STRENGTHS

ULSPIRA (nitric oxide) gas is available in a 800 ppm concentration.

4 CONTRAINDICATIONS

ULSPIRA is contraindicated in neonates dependent on right-to-left shunting of blood.

5 WARNINGS AND PRECAUTIONS

5.1 Rebound Pulmonary Hypertension Syndrome following Abrupt Discontinuation

Wean from ULSPIRA [see Dosage and Administration (2.2)].Abrupt discontinuation of ULSPIRA may lead to worsening oxygenation and increasing pulmonary artery pressure, i.e., Rebound Pulmonary Hypertension Syndrome. Signs and symptoms of Rebound Pulmonary Hypertension Syndrome include hypoxemia, systemic hypotension, bradycardia, and decreased cardiac output. If Rebound Pulmonary Hypertension occurs, reinstate ULSPIRA therapy immediately.

5.2 Hypoxemia from Methemoglobinemia

Nitric oxide combines with hemoglobin to form methemoglobin, which does not transport oxygen. Methemoglobin levels increase with the dose of ULSPIRA; it can take 8 hours or more before steady-state methemoglobin levels are attained. Monitor methemoglobin and adjust the dose of ULSPIRA to optimize oxygenation.

If methemoglobin levels do not resolve with decrease in dose or discontinuation of ULSPIRA, additional therapy may be warranted to treat methemoglobinemia [see Overdosage (10)].

5.3 Airway Injury from Nitrogen Dioxide

Nitrogen dioxide (NO2) forms in gas mixtures containing NO and O2. Nitrogen dioxide may cause airway inflammation and damage to lung tissues.

If there is an unexpected change in NO2 concentration, or if the NO2 concentration reaches 3 ppm when measured in the breathing circuit, then the delivery system should be assessed in accordance with the Nitric Oxide Delivery System O&M Manual troubleshooting section, and the NO2 analyzer should be recalibrated. The dose of ULSPIRA and/or FiO2 should be adjusted as appropriate.

5.4 Worsening Heart Failure

Patients with left ventricular dysfunction treated with ULSPIRA may experience pulmonary edema, increased pulmonary capillary wedge pressure, worsening of left ventricular dysfunction, systemic hypotension, bradycardia and cardiac arrest. Discontinue ULSPIRA gas while providing symptomatic care.

6 ADVERSE REACTIONS

The following adverse reactions are discussed elsewhere in the label;

Hypoxemia [see Warnings and Precautions (5.2)]

Worsening Heart Failure [see Warnings and Precautions (5.4)]

6.1 Clinical Trials Experience

Because clinical trials are conducted under widely varying conditions, adverse reaction rates observed in the clinical trials of a drug cannot be directly compared to rates in the clinical trials of another drug and may not reflect the rates observed in practice. The adverse reaction information from the clinical studies does, however, provide a basis for identifying the adverse events that appear to be related to drug use and for approximating rates.

Controlled studies have included 325 patients on nitric oxide doses of 5 to 80 ppm and 251 patients on placebo. Total mortality in the pooled trials was 11% on placebo and 9% on nitric oxide, a result adequate to exclude nitric oxide mortality being more than 40% worse than placebo.

In both the NINOS and CINRGI studies, the duration of hospitalization was similar in nitric oxide and placebo-treated groups.

From all controlled studies, at least 6 months of follow-up is available for 278 patients who received nitric oxide and 212 patients who received placebo. Among these patients, there was no evidence of an adverse effect of treatment on the need for rehospitalization, special medical services, pulmonary disease, or neurological sequelae.

In the NINOS study, treatment groups were similar with respect to the incidence and severity of intracranial hemorrhage, Grade IV hemorrhage, periventricular leukomalacia, cerebral infarction, seizures requiring anticonvulsant therapy, pulmonary hemorrhage, or gastrointestinal hemorrhage.

In CINRGI, the only adverse reaction (>2% higher incidence on nitric oxide than on placebo) was hypotension (14% vs. 11%).

6.2 Post-Marketing Experience

Post marketing reports of accidental exposure to nitric oxide for inhalation in hospital staff has been associated with chest discomfort, dizziness, dry throat, dyspnea, and headache.

7 DRUG INTERACTIONS

7.1 Nitric Oxide Donor Agents

Nitric oxide donor agents such as prilocaine, sodium nitroprusside and nitroglycerine may increase the risk of developing methemoglobinemia.

8 USE IN SPECIFIC POPULATIONS

8.4 Pediatric Use

The safety and efficacy of nitric oxide for inhalation has been demonstrated in term and near- term neonates with hypoxic respiratory failure associated with evidence of pulmonary hypertension [see Clinical Studies (14.1)].Additional studies conducted in premature neonates for the prevention of bronchopulmonary dysplasia have not demonstrated substantial evidence of efficacy [see Clinical Studies (14.3)].No information about its effectiveness in other age populations is available.

8.5 Geriatric Use

Nitric oxide is not indicated for use in the adult population.

10 OVERDOSAGE

Overdosage with nitric oxide is manifest by elevations in methemoglobin and pulmonary toxicities associated with inspired NO2. Elevated NO2 may cause acute lung injury. Elevations in methemoglobin reduce the oxygen delivery capacity of the circulation. In clinical studies, NO2 levels >3 ppm or methemoglobin levels >7% were treated by reducing the dose of, or discontinuing, nitric oxide.

Methemoglobinemia that does not resolve after reduction or discontinuation of therapy can be treated with intravenous vitamin C, intravenous methylene blue, or blood transfusion, based upon the clinical situation.

11 DESCRIPTION

ULSPIRA (nitric oxide gas) is adrug administered by inhalation. Nitric oxide, the active substance in ULSPIRA, is a pulmonary vasodilator. ULSPIRA is a gaseous blend of nitric oxide and nitrogen (0.08% and 99.92%, respectively for 800 ppm).

ULSPIRA is supplied in aluminum cylinders as a compressed gas under high pressure (2000 pounds per square inch gauge [psig]).

The structural formula of nitric oxide (NO) is shown below:

12 CLINICAL PHARMACOLOGY

12.1 Mechanism of Action

Nitric oxide relaxes vascular smooth muscle by binding to the heme moiety of cytosolic guanylate cyclase, activating guanylate cyclase and increasing intracellular levels of cyclic guanosine 3',5'-monophosphate, which then leads to vasodilation. When inhaled, nitric oxide selectively dilates the pulmonary vasculature, and because of efficient scavenging by hemoglobin, has minimal effect on the systemic vasculature.

Nitric oxide appears to increase the partial pressure of arterial oxygen (PaO2) by dilating pulmonary vessels in better ventilated areas of the lung, redistributing pulmonary blood flow away from lung regions with low ventilation/perfusion (V/Q) ratios toward regions with normal ratios.

12.2 Pharmacodynamics

Effects on Pulmonary Vascular Tone in PPHN

Persistent pulmonary hypertension of the newborn (PPHN) occurs as a primary developmental defect or as a condition secondary to other diseases such as meconium aspiration syndrome (MAS), pneumonia, sepsis, hyaline membrane disease, congenital diaphragmatic hernia (CDH), and pulmonary hypoplasia. In these states, pulmonary vascular resistance (PVR) is high, which results in hypoxemia secondary to right-to-left shunting of blood through the patent ductus arteriosus and foramen ovale. In neonates with PPHN, nitric oxide improves oxygenation (as indicated by significant increases in PaO2).

12.3 Pharmacokinetics

The pharmacokinetics of nitric oxide has been studied in adults.

Absorption and Distribution

Nitric oxide is absorbed systemically after inhalation. Most of it traverses the pulmonary capillary bed where it combines with hemoglobin that is 60% to 100% oxygen-saturated. At this level of oxygen saturation, nitric oxide combines predominantly with oxyhemoglobin to produce methemoglobin and nitrate. At low oxygen saturation, nitric oxide can combine with deoxyhemoglobin to transiently form nitrosylhemoglobin, which is converted to nitrogen oxides and methemoglobin upon exposure to oxygen. Within the pulmonary system, nitric oxide can combine with oxygen and water to produce nitrogen dioxide and nitrite, respectively, which interact with oxyhemoglobin to produce methemoglobin and nitrate. Thus, the end products of nitric oxide that enter the systemic circulation are predominantly methemoglobin and nitrate.

Metabolism

Methemoglobin disposition has been investigated as a function of time and nitric oxide exposure concentration in neonates with respiratory failure. The methemoglobin (MetHb) concentration- time profiles during the first 12 hours of exposure to 0, 5, 20, and 80 ppm nitric oxide are shown in Figure 1.

Figure 1: Methemoglobin Concentration-Time Profiles Neonates Inhaling 0, 5, 20 or 80 ppm Nitric Oxide

Methemoglobin concentrations increased during the first 8 hours of nitric oxide exposure. The mean methemoglobin level remained below 1% in the placebo group and in the 5 ppm and 20 ppm nitric oxide groups, but reached approximately 5% in the 80 ppm nitric oxide group.

Methemoglobin levels >7% were attained only in patients receiving 80 ppm, where they comprised 35% of the group. The average time to reach peak methemoglobin was 10 ± 9 (SD) hours (median, 8 hours) in these 13 patients, but one patient did not exceed 7% until 40 hours.

Elimination

Nitrate has been identified as the predominant nitric oxide metabolite excreted in the urine, accounting for >70% of the nitric oxide dose inhaled. Nitrate is cleared from the plasma by the kidney at rates approaching the rate of glomerular filtration.

13 NONCLINICAL TOXICOLOGY

13.1 Carcinogenesis, Mutagenesis, Impairment of Fertility

No evidence of a carcinogenic effect was apparent, at inhalation exposures up to the recommended dose (20 ppm), in rats for 20 hr/day for up to two years. Higher exposures have not been investigated.

Nitric oxide has demonstrated genotoxicity in Salmonella (Ames Test), human lymphocytes, and after in vivoexposure in rats. There are no animal or human studies to evaluate nitric oxide for effects on fertility.

14 CLINICAL STUDIES

14.1 Treatment of Hypoxic Respiratory Failure (HRF)

The efficacy of nitric oxide has been investigated in term and near-term newborns with hypoxic respiratory failure resulting from a variety of etiologies. Inhalation of nitric oxide reduces the oxygenation index (OI= mean airway pressure in cm H2O × fraction of inspired oxygen concentration [FiO2]× 100 divided by systemic arterial concentration in mm Hg [PaO2]) and increases PaO2 [see Clinical Pharmacology (12.1)].

 | Control; (n=121) | NO; (n=114) | P value
Death or ECMO*,† | 77 (64%) | 52 (46%) | 0.006
Death | 20 (17%) | 16 (14%) | 0.60
ECMO | 66 (55%) | 44 (39%) | 0.014

 | Placebo | Nitric Oxide | P value
ECMO*,† | 51/89 (57%) | 30/97 (31%) | <0.001
Death | 5/89 (6%) | 3/97 (3%) | 0.48

14.3 Ineffective in Prevention of Bronchopulmonary Dysplasia (BPD)

The safety and efficacy of nitric oxide for the prevention of chronic lung disease [bronchopulmonary dysplasia, (BPD)] in neonates ≤ 34 weeks gestational age requiring respiratory support has been studied in four large, multi-center, double-blind, placebo-controlled clinical trials in a total of 2,600 preterm infants. Of these, 1,290 received placebo, and 1,310 received inhaled nitric oxide at doses ranging from 5-20 ppm, for treatment periods of 7-24 days duration. The primary endpoint for these studies was alive and without BPD at 36 weeks postmenstrual age (PMA). The need for supplemental oxygen at 36 weeks PMA served as a surrogate endpoint for the presence of BPD. Overall, efficacy for the prevention of bronchopulmonary dysplasia in preterm infants was not established. There were no meaningful differences between treatment groups with regard to overall deaths, methemoglobin levels, or adverse events commonly observed in premature infants, including intraventricular hemorrhage, patent ductus arteriosus, pulmonary hemorrhage, and retinopathy of prematurity.

The use of nitric oxide for prevention of BPD in preterm neonates ≤ 34 weeks gestational age is not recommended.

16 HOW SUPPLIED/STORAGE AND HANDLING

Size D | Portable aluminum cylinders containing 362 liters at STP of nitric oxide gas in 800 ppm concentration in nitrogen (delivered volume 350 liters) (NDC 82605-006-02)
Size 88 | Aluminum cylinders containing 2138 liters at STP of nitric oxide gas in 800 ppm concentration in nitrogen (delivered volume 2083 liters) (NDC 82605-006-01)

Distributed by

Airgas Therapeutics LLC Radnor, PA 19087 USA

AirGas Therapeutics

an Air Liquide company

© 2023 Airgas

ULSPI 01

PACKAGE LABEL

Ulspira TM

(nitric oxide for inhalation)

800 PPM

Rx Only

CAUTION: HIGH PRESSURE GAS. CAN CAUSE RAPID SUFFOCATION WITHOUT WARNING. Use equipment rated for cylinder pressure. Store and use with adequate ventilation. Secure cylinder in use and storage. Close valve after each use and when empty. USE IN ACCORDANCE WITH APPROPRIATE SDS.

WARNING: Administration of this gas mixture may be hazardous or contraindicated. For use only by or under the supervision of a licensed practitioner who is experienced in the use and administration of gas mixtures, and is familiar with the indications, effects, dosages, methods, and frequency and duration of administration, and with the hazards, contraindications, and side effects and the precautions to be taken.

FIRST AID: IF INHALED, remove person to fresh air. If not breathing, give artificial respiration. If breathing is difficult, give oxygen. Get medical help.

RETURN WITH 25 PSIG.

TO BE REFILLED ONLY BY A PHARMACEUTICAL FACILITY

AUTHORIZED BY AIRGAS THERAPEUTICS, LLC

Manufactured Under Pharmaceutical Current Good Manufacturing Practices (cGmps).

DO NOT REMOVE THIS PRODUCT LABEL

Store at 25 C (77 F) with excursions permitted between 15 – 30 C (59 – 86 F).

Volume 2138 Liters

Airgas Therapeutics

An Air Liquide company

Manufactured by:

AIRGAS THERAPEUTICS, LLC

6141 Easton Road

Plumsteadville, PA 18949-0310

For Product Inquiry 1-833-ULSPIRA (857-7472)

UN1956

COMPRESSED GAS, N.O.S. (NITRIC OXIDE, NITROGEN) 2.2

Net Weight: 2.5 kg

LOT:

EXP:

NDC 82605-006-01

PACKAGE LABEL

Ulspira TM

(nitric oxide for inhalation)

800 PPM

Rx Only

CAUTION: HIGH PRESSURE GAS. CAN CAUSE RAPID SUFFOCATION WITHOUT WARNING. Use equipment rated for cylinder pressure. Store and use with adequate ventilation. Secure cylinder in use and storage. Close valve after each use and when empty. USE IN ACCORDANCE WITH APPROPRIATE SDS.

WARNING: Administration of this gas mixture may be hazardous or contraindicated. For use only by or under the supervision of a licensed practitioner who is experienced in the use and administration of gas mixtures, and if familiar with the indications, effects, dosages, methods, and frequency and duration of administration, and with the hazards, contraindications and side effects and the precautions to be taken.

FIRST AID: IF INHALED, remove person to fresh air. If not breathing, give artificial respiration. If breathing is difficult, give oxygen. Get medical help.

RETURN WITH 25 PSIG.

TO BE REFILLED ONLY BY A PHARMACEUTICAL FACILITY

AUTHORIZED BY AIRGAS THERAPEUTICS, LLC

Manufactured Under Pharmaceutical Current Good Manufacturing Practices (cGMPs).

DO NOT REMOVE THIS PRODUCT LABELS

Store at 25 C (77 F) with excursions permitted between 15 - 30 C (59 – 86 F).

Volume 362 Liters

Airgas Therapeutics

An Air Liquide company

Manufactured by:

AIRGAS THERAPEUTICS, LLC

6141

Easton Road

Plumsteadville, PA 18949-0310

For Product Inquiry 1-833-ULSPIRA (857-7472)

UN 1956

COMPRESSED GAS, N.O.S. (NITRIC OXIDE, NITROGEN) 2.2

Net Weight: 0.4 kg

LOT:

EXP:

NDC 82605-006-02